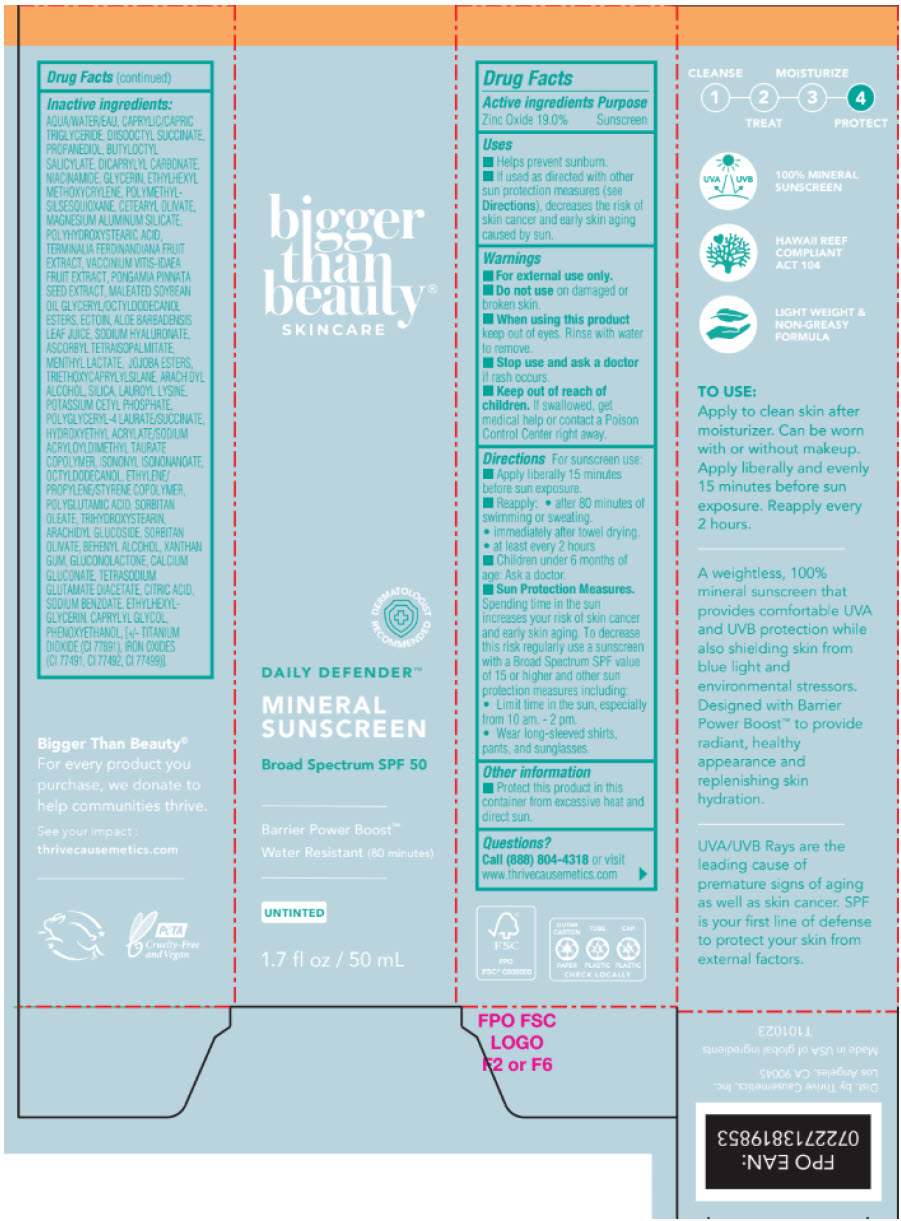 DRUG LABEL: Daily Defender Mineral Sunscreen Broad Spectrum SPF 50 Water Resistant (80 minutes)
NDC: 77365-009 | Form: CREAM
Manufacturer: Thrive Causemetics
Category: otc | Type: HUMAN OTC DRUG LABEL
Date: 20240814

ACTIVE INGREDIENTS: Zinc Oxide 190 mg/1 mL
INACTIVE INGREDIENTS: WATER; MEDIUM-CHAIN TRIGLYCERIDES; DIISOBUTYL SUCCINATE; PROPANEDIOL; BUTYLOCTYL SALICYLATE; DICAPRYLYL CARBONATE; NIACINAMIDE; GLYCERIN; ETHYLHEXYL METHOXYCRYLENE; POLYMETHYLSILSESQUIOXANE (4.5 MICRONS); CETEARYL OLIVATE; MAGNESIUM ALUMINUM SILICATE; POLYHYDROXYSTEARIC ACID (2300 MW); KAKADU PLUM; LINGONBERRY; PONGAMIA PINNATA SEED; SOYBEAN OIL GLYCERETH-8 ESTERS; ECTOINE; ALOE VERA LEAF; HYALURONATE SODIUM; ASCORBYL TETRAISOPALMITATE; MENTHYL LACTATE, (-)-; JOJOBA OIL, RANDOMIZED; TRIETHOXYCAPRYLYLSILANE; ARACHIDYL ALCOHOL; SILICON DIOXIDE; LAUROYL LYSINE; POTASSIUM CETYL PHOSPHATE; POLYGLYCERYL-4 LAURATE/SUCCINATE; HYDROXYETHYL ACRYLATE/SODIUM ACRYLOYLDIMETHYL TAURATE COPOLYMER (100000 MPA.S AT 1.5%); ISONONYL ISONONANOATE; OCTYLDODECANOL; STYRENE/ISOPRENE COPOLYMER (28:72; 210000 MW); POLYGLUTAMIC ACID (8000 MW); SORBITAN MONOOLEATE; TRIHYDROXYSTEARIN; ARACHIDYL GLUCOSIDE; SORBITAN OLIVATE; DOCOSANOL; XANTHAN GUM; GLUCONOLACTONE; CALCIUM GLUCONATE; TETRASODIUM GLUTAMATE DIACETATE; CITRIC ACID MONOHYDRATE; SODIUM BENZOATE; ETHYLHEXYLGLYCERIN; CAPRYLYL GLYCOL; PHENOXYETHANOL; TITANIUM DIOXIDE; FERRIC OXIDE RED; FERRIC OXIDE YELLOW; FERROSOFERRIC OXIDE

Daily Defender™ Mineral Sunscreen Broad Spectrum SPF 50 Water Resistant (80 minutes)

Drug Facts

Active ingredient

Zinc Oxide 19.0%

Purpose

Sunscreen

Uses

- Helps prevent sunburn
- If used as directed with other sun protection measures (see Directions), decreases the risk Skin cancer and early skin aging caused by the sun.

Warnings

- For external use only.

Do not use

- on damaged or broken skin.

When using this product

- keep out of eyes. Rinse with water to remove.

Stop use and ask a doctor if

- rash occurs.

Keep out of reach of children.

- If swallowed, get medical help or contact a Poison Control Center right away.

Directions

For sunscreen use:

- Apply liberally 15 minutes before sun exposure.
- reapply:
  - after 80 minutes of swimming or sweating
  - immediately after towel drying
  - at least every 2 hours.
- Children under 6 months of age: Ask a doctor.
- Sun Protection Measures: Spending time in the sun increases your risk of skin cancer and early skin aging. To decrease this risk regularly use a sunscreen with a Broad Spectrum SPF value of 15 or higher and other sun protection measures including:
  - Limit time in the sun, especially from 10 am. - 2 pm.
  - Wear long-sleeved shirts, pants, and sunglasses.

Other information

- Protect this product in this container from excessive heat and direct sun.

Questions?

Call (888) 804-4318 or visit www.thrivecausemetics.com

Inactive ingredients

AQUA/WATER/EAU, CAPRYLIC/CAPRIC TRIGLYCERIDE, DIISOOCTYL SUCCINATE, PROPANEDIOL, BUTYLOCTYL SALICYLATE, DICAPRYLYL CARBONATE, NIACINAMIDE, GLYCERIN, ETHYLHEXYL METHOXYCRYLENE, POLYMETHYLSILSESQUIOXANE, CETEARYL OLIVATE, MAGNESIUM ALUMINUM SILICATE, POLYHYDROXYSTEARIC ACID, TERMINALIA FERDINANDIANA FRUIT EXTRACT, VACCINIUM VITIS-IDAEA FRUIT EXTRACT, PONGAMIA PINNATA SEED EXTRACT, MALEATED SOYBEAN OIL GLYCERYL/OCTYLDODECANOL ESTERS, ECTOIN, ALOE BARBADENSIS LEAF JUICE, SODIUM HYALURONATE, ASCORBYL TETRAISOPALMITATE, MENTHYL LACTATE, JOJOBA ESTERS, TRIETHOXYCAPRYLYLSILANE, ARACHIDYL ALCOHOL, SILICA, LAUROYL LYSINE, POTASSIUM CETYL PHOSPHATE, POLYGLYCERYL-4 LAURATE/SUCCINATE, HYDROXYETHYL ACRYLATE/SODIUM ACRYLOYLDIMETHYL TAURATE COPOLYMER, ISONONYL ISONONANOATE, OCTYLDODECANOL, ETHYLENE/PROPYLENE/STYRENE COPOLYMER, POLYGLUTAMIC ACID, SORBITAN OLEATE, TRIHYDROXYSTEARIN, ARACHIDYL GLUCOSIDE, SORBITAN OLIVATE, BEHENYL ALCOHOL, XANTHAN GUM, GLUCONOLACTONE, CALCIUM GLUCONATE, TETRASODIUM GLUTAMATE DIACETATE, CITRIC ACID, SODIUM BENZOATE, ETHYLHEXYLGLYCERIN, CAPRYLYL GLYCOL, PHENOXYETHANOL, [+/- TITANIUM DIOXIDE (CI 77891), IRON OXIDES (CI 77491, CI 77492, CI 77499)].

Dist. by Thrive Causemetics, Inc.
Los Angeles, CA 90045

PRINCIPAL DISPLAY PANEL - 50 mL Tube Box

bigger
than
beauty®
SKINCARE

DERMATOLOGIST
RECOMMENDED

DAILY DEFENDER™

MINERAL
SUNSCREEN

Broad Spectrum SPF 50

Barrier Power Boost™

Water Resistant (80 minutes)

UNTINTED

1.7 fl oz / 50 mL